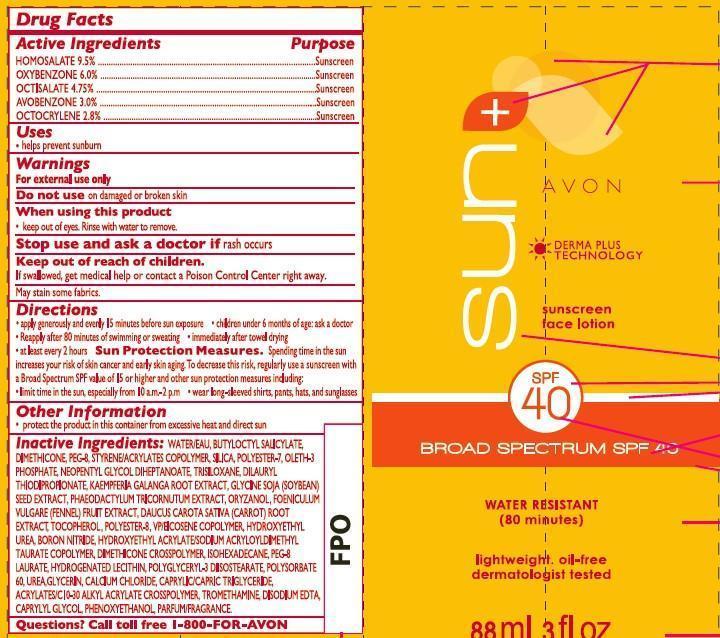 DRUG LABEL: Avon Sun
NDC: 10096-0294 | Form: LOTION
Manufacturer: Avon Products, Inc
Category: otc | Type: HUMAN OTC DRUG LABEL
Date: 20130327

ACTIVE INGREDIENTS: HOMOSALATE 95 mg/1 mL; OXYBENZONE 60 mg/1 mL; OCTISALATE 47.5 mg/1 mL; AVOBENZONE 30 mg/1 mL; OCTOCRYLENE 28 mg/1 mL

Active ingredients
HOMOSALATE 9.5%..................

OXYBENZONE 6.0%.....................

OCTISALATE 4.75%.....................

AVOBENZONE 3.0%...................

OCTOCRYLENE 2.8%..................

Purpose
.................................Sunscreen

.................................Sunscreen

.................................Sunscreen

.................................Sunscreen

.................................Sunscreen

Uses
• helps prevent sunburn

Warnings
For external use only

Do not use on damaged or broken skin

When using this product

- keep out of eyes. Rinse with water to remove.

Stop use and ask a doctor if rash occurs

Keep out of reach of children.

If swallowed, get medical help or contact a Poison Control Center right away.

Directions
• apply generously and evenly 15 minutes before sun exposure
• children under 6 months of age: ask a doctor
• reapply after 80 minutes of swimming or sweating
• immediately after towel drying

• at least every 2 hours

• Sun Protection Measures. Spending time in the sun increases your risk of skin cancer and early skin aging. To decrease this risk, regularly use a sunscreen with a Broad Spectrum SPF value of 15 or higher and other sun protection measures including:
• limit time in the sun, especially from 10 a.m. – 2 p.m.
• wear long-sleeved shirts, pants, hats, and sunglasses

Other information

• protect the product in this container from excessive heat and direct sun

Inactive Ingredients:
WATER/EAU, BUTYLOCTYL SALICYLATE, DIMETHICONE, PEG-8, STYRENE/ACRYLATES COPOLYMER, SILICA, POLYESTER-7, OLETH-3 PHOSPHATE, NEOPENTYL GLYCOL DIHEPTANOATE, TRISILOXANE, DILAURYL THIODIPROPIONATE, KAEMPFERIA GALANGA ROOT EXTRACT, GLYCINE SOJA (SOYBEAN) SEED EXTRACT, PHAEODACTYLUM TRICORNUTUM EXTRACT, ORYZANOL, FOENICULUM VULGARE (FENNEL) FRUIT EXTRACT, DAUCUS CAROTA SATIVA (CARROT) ROOT EXTRACT, TOCOPHEROL, POLYESTER-8, VP/EICOSENE COPOLYMER, HYDROXYETHYL UREA, BORON NITRIDE, HYDROXYETHYL ACRYLATES/SODIUM ACRYLOYLDIMETHYL TAURATE COPOLYMER, DIMETHICONE CROSSPOLYMER, ISOHEXADECANE, PEG-8 LAURATE, HYDROGENATED LECITHIN, POLYGLYCERYL-3 DIISOSTEARATE, POLYSORBATE 60, UREA, GLYCERIN, CALCIUM CHLORIDE, CARYLIC/CAPRIC TRIGLYCERIDE, ACRYLATES/C10-30 ALKYL ACRYLATE CROSSPOLYMER, TROMETHAMINE, DISODIUM EDTA, CAPRYLYL GLYCOL, PHENOXYETHANOL, PARFUM/FRAGRANCE

Questions?
Call toll free 1-800-FOR-AVON